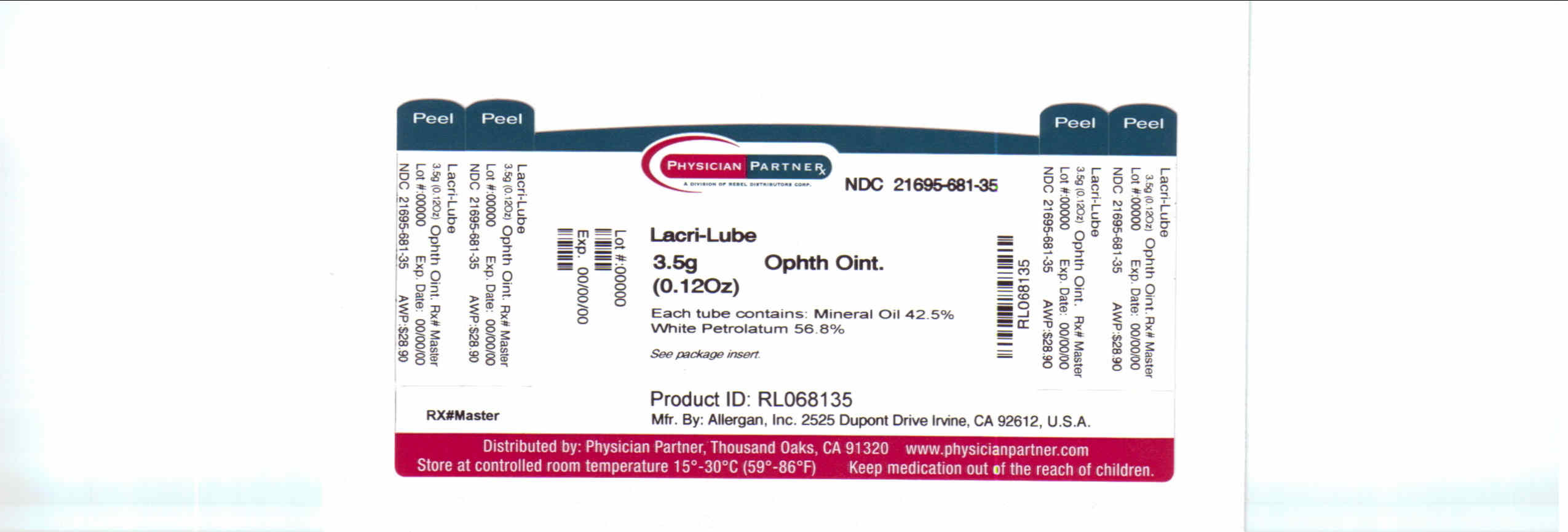 DRUG LABEL: Mineral Oil
NDC: 21695-681 | Form: OINTMENT
Manufacturer: Rebel Distributors Corp
Category: otc | Type: HUMAN OTC DRUG LABEL
Date: 20110217

ACTIVE INGREDIENTS: MINERAL OIL 425 mg/1 g; PETROLATUM 568 mg/1 g
INACTIVE INGREDIENTS: CHLOROBUTANOL; LANOLIN ALCOHOLS

Lacri-Lube Drug Facts

Active ingredient

Mineral Oil 42.5%

White Petrolatum 56.8%

Purpose

Eye lubricant

Keep Out of Reach of Children

If swallowed, get medical help or contact a Poison Control Center right away.

Uses

For use as a protectant against further irritation or to relieve dryness or the eye.

Warnings

For external use only.

To avoid contamination, do not touch tip of container to any surface.

Replace cap after using.

Stop use and ask a doctor if you experience eye pain, changes in vision, continued redness or irritation of the eye, or if the condition worsens or persists for more than 72 hours.

Directions

Pull down the lower lid of the affected eye and apply a small amount (one-fourth inch) of ointment to the inside of the eyelid.

Other Information

Use only if imprinted tape seals on top and bottom flaps are intact and clearly legible.

Store away from heat. Protect from freezing.

Use before expiration date marked on container.

RETAIN THIS CARTON FOR FUTURE REFERENCE.

Inactive ingredients

Chlorobutanol and lanolin alcohols.